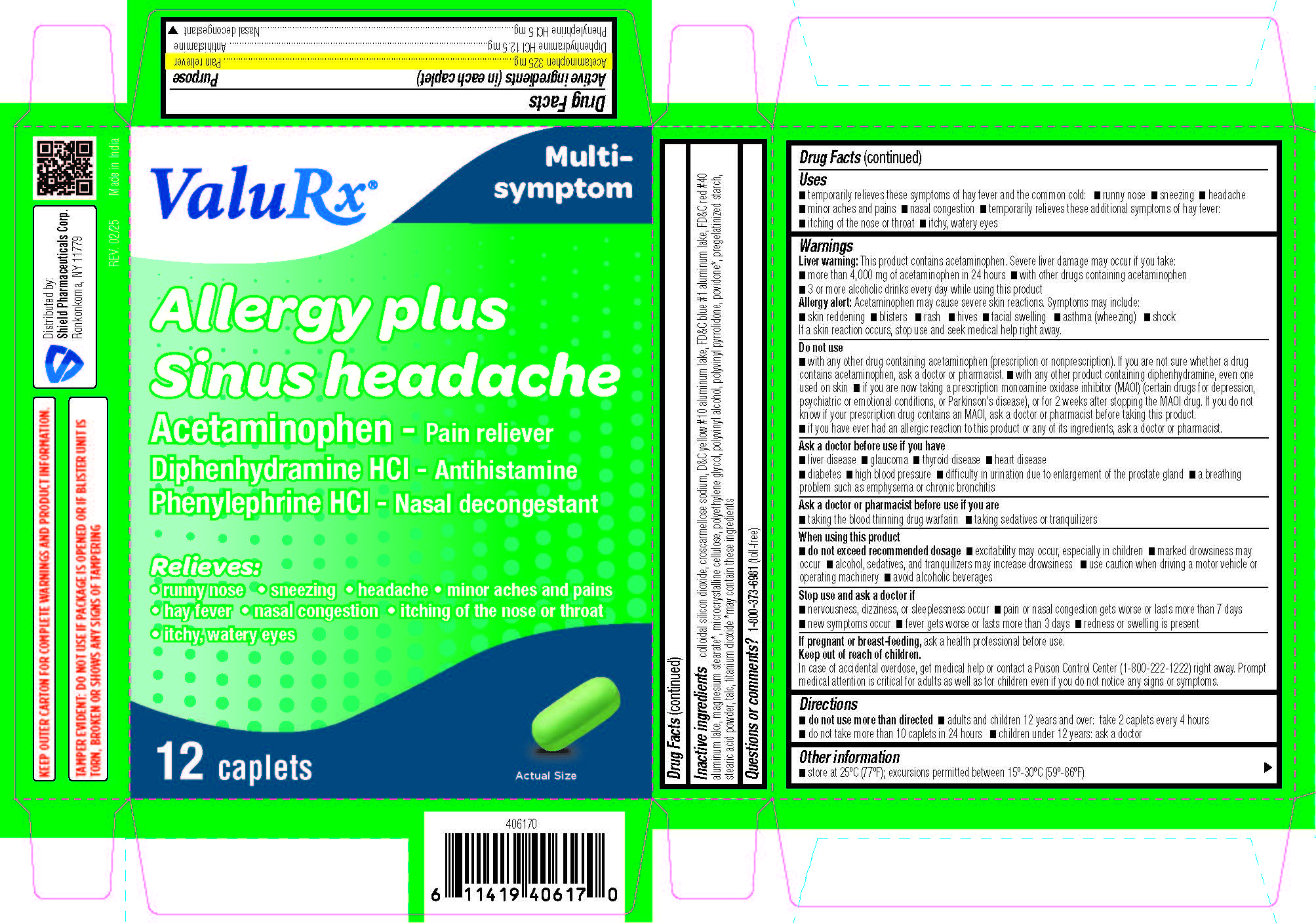 DRUG LABEL: Allergy plus Sinus Headache
NDC: 83059-0106 | Form: TABLET, FILM COATED
Manufacturer: Shield Pharmaceuticals Corp
Category: otc | Type: HUMAN OTC DRUG LABEL
Date: 20251107

ACTIVE INGREDIENTS: ACETAMINOPHEN 325 mg/1 1; DIPHENHYDRAMINE HYDROCHLORIDE 12.5 mg/1 1; PHENYLEPHRINE HYDROCHLORIDE 5 mg/1 1
INACTIVE INGREDIENTS: STARCH, CORN; CROSCARMELLOSE SODIUM; POVIDONE; D&C YELLOW NO. 10; FD&C BLUE NO. 1; FD&C RED NO. 40; MAGNESIUM STEARATE; MICROCRYSTALLINE CELLULOSE; POLYETHYLENE GLYCOL, UNSPECIFIED; POLYVINYL ALCOHOL, UNSPECIFIED; SILICON DIOXIDE; STEARIC ACID; TALC; TITANIUM DIOXIDE

Allergy plus Sinus Headache

Drug Facts

Active ingredient (in each liquid-filled capsule)

Acetaminophen 325 mg

Diphenhydramine HCl 12.5 mg

Phenylephrine HCl 5 mg

Purpose

Pain reliever

Antihistamine

Nasal decongestant

Uses

- temporarily relieves these symptoms of hay fever and the common cold:
- runny nose
- sneezing
- headache
- minor aches and pains
- nasal congestion
- temporarily relieves these additional symptoms of hay fever:
- itching of the nose or throat
- itchy, watery eyes

Warnings

Liver warning:This product contains acetaminophen. Severe liver damage may occur if you take:

- more than 4,000 mg of acetaminophen in 24 hours
- with other drugs containing acetaminophen
- 3 or more alcoholic drinks every day while using this product

Allergy alert:Acetaminophen may cause severe skin reactions.

Symptoms may include:

- skin reddening
- blisters
- rash
- hives
- facial swelling
- asthma (wheezing)
- shock

If a skin reaction occurs, stop use and seek medical help right away.

Do not use

- with any other drug containing acetaminophen (prescription or nonprescription). If you are not sure whether a drug contains acetaminophen, ask a doctor or pharmacist.
- with any other product containing diphenhydramine, even one used on skin
- if you are now taking a prescription monoamine oxidase inhibitor (MAOI) (certain drugs for depression, psychiatric or emotional conditions, or Parkinson's disease), or for 2 weeks after stopping the MAOI drug. If you do not know if your prescription drug contains an MAOI, ask a doctor or pharmacist before taking this product.
- if you have ever had an allergic reaction to this product or any of its ingredients acetaminophen, ask a doctor or pharmacist.

Ask a doctor before use if you have

- liver disease
- glaucoma
- thyroid disease
- heart disease
- diabetes
- high blood pressure
- difficulty in urination due to enlargement of the prostate gland
- a breathing problem such as emphysema or chronic bronchitis

Ask a doctor or pharmacist before use if you are

- taking the blood thinning drug warfarin
- taking sedatives or tranquilizers

When using this product

- do not exceed recommended dosage
- excitability may occur, especially in children
- marked drowsiness may occur
- alcohol, sedatives, and tranquilizers may increase drowsiness
- use caution when driving a motor vehicle or operating machinery
- avoid alcoholic beverages

Stop use and ask a doctor if

- nervousness, dizziness, or sleeplessness occur
- pain or nasal congestion gets worse or lasts more than 7 days
- new symptoms occur
- fever gets worse or lasts more than 3 days
- redness or swelling is present

PREGNANCY OR BREAST FEEDING

If pregnant or breast-feeding, ask a health professional before use.

Keep out of reach of children. In case of overdose, get medical help or contact a Poison Control Center right away.1(800)222-1222

Directions

- do not use more than directed
- adults and children 12 years and over: take 2 caplets every 4 hours
- do not take more than 10 caplets in 24 hours
- children under 12 years: ask a doctor

Other information

- store at 25ºC (77ºF); excursions permitted between 15º-30ºC (59º-86ºF)

TAMPER EVIDENT: DO NOT USE IF CARTON IS OPENED OR SAFETY SEAL UNDER CAP IS BROKEN OR MISSING.

KEEP OUTER CARTON FOR COMPLETE WARNINGS AND PRODUCT INFORMATION.

Inactive ingredients

colloidal silicon dioxide, croscarmellose sodium, D&C yellow #10 aluminum lake, FD&C blue #1 aluminum lake, FD&C red #40 aluminum lake, magnesium stearate*, microcrystalline cellulose, polyethylene glycol, polyvinyl alcohol, polyvinyl pyrrolidone, povidone*, pregelatinized starch, stearic acid powder, talc, titanium dioxide *may contain these ingredients

Questions or comments?

1-800-373-6981 (toll-free)

Distributed by:

Shield Pharmaceuticals Corp.

Ronkonkoma, NY 11779

PRINCIPAL DISPLAY PANEL

Allergy plus Sinus headache

Acetaminophen

Diphenhydramine HCl

Phenylephrine HCl

Pain reliever / Antihistamine / Nasal decongestant

Relieves:
runny nose • sneezing • headache
• minor aches and pains • hay fever
• nasal congestion • itching of the nose or throat
• itchy, watery eyes

Carton